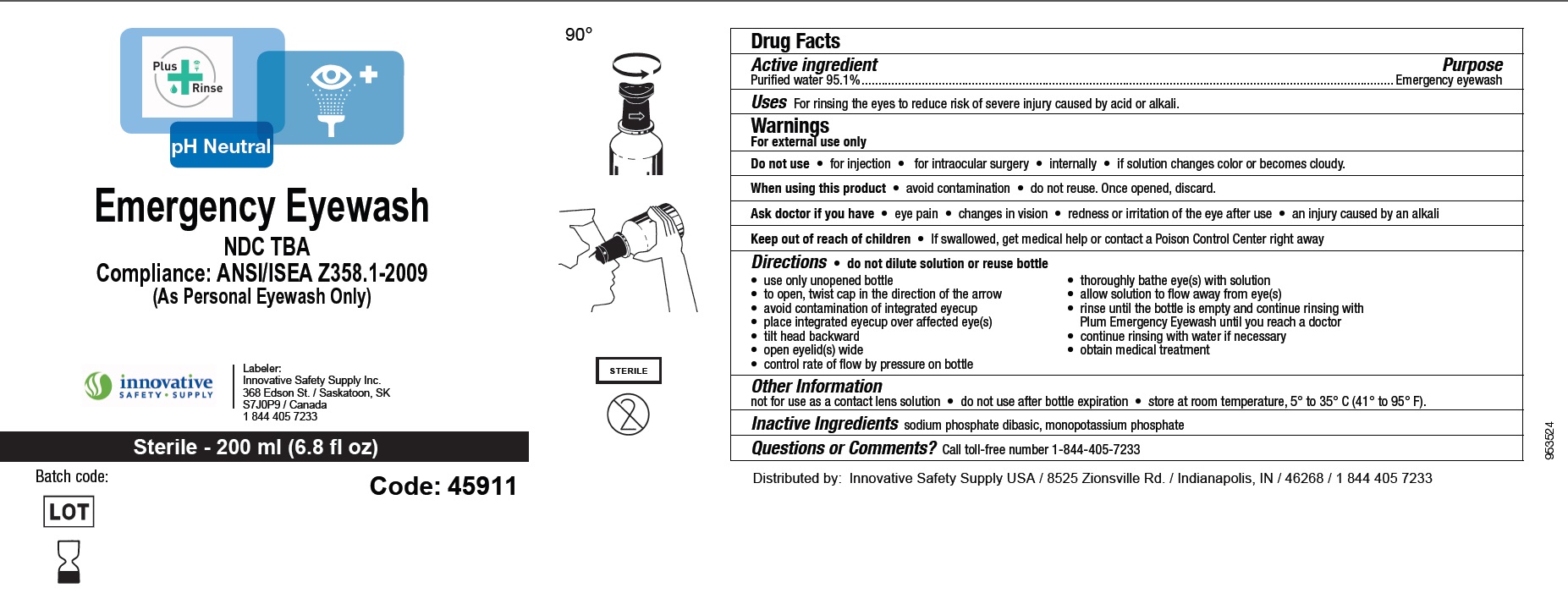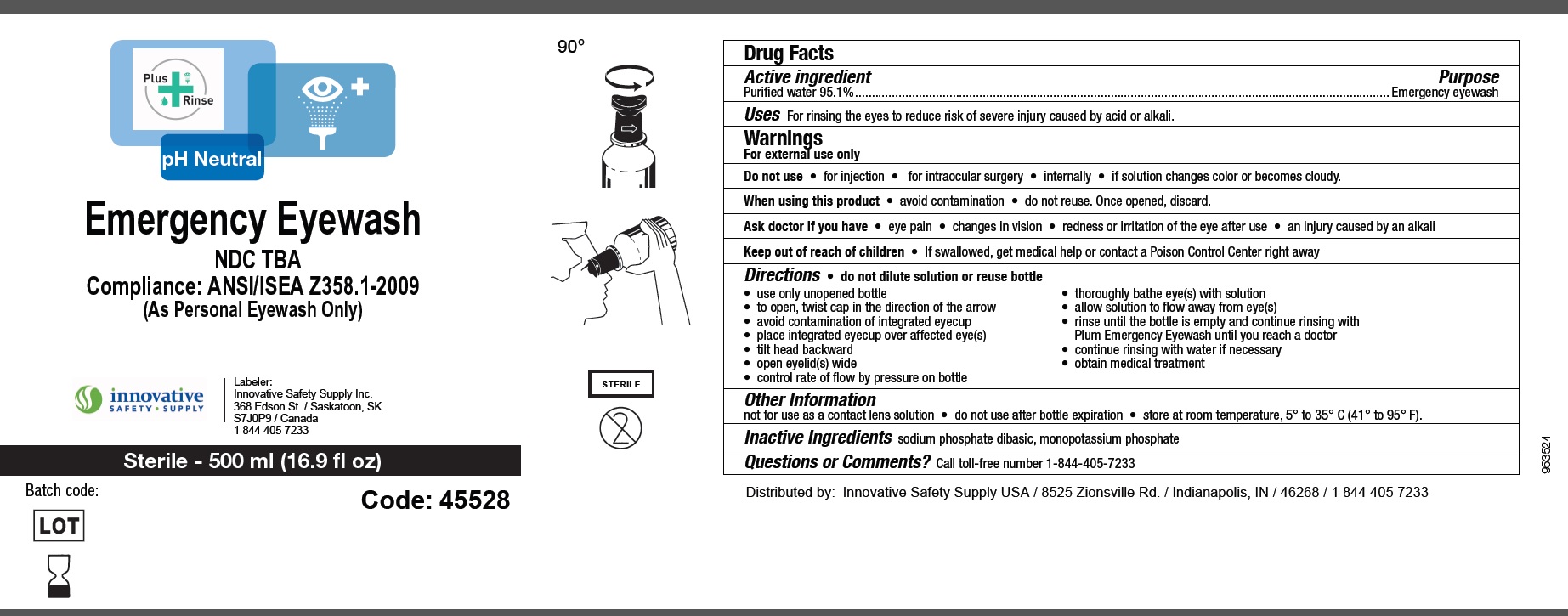 DRUG LABEL: pH Neutral Emergency Eyewash
NDC: 72598-095 | Form: LIQUID
Manufacturer: INNOVATIVE SAFETY SUPPLY INC.
Category: otc | Type: HUMAN OTC DRUG LABEL
Date: 20241219

ACTIVE INGREDIENTS: WATER 95.1 mL/100 mL
INACTIVE INGREDIENTS: SODIUM PHOSPHATE, DIBASIC; POTASSIUM PHOSPHATE, MONOBASIC

Drug Facts

Active ingredient

Purified water 95.1%

Purpose

Emergency eyewash

Uses

For rinsing the eyes to reduce risk of severe injury caused by acid or alkali

Warnings

For external use only

Do not use

● for injection

● for intraocular surgery

● internally

● If solution changes color or becomes cloudy.

When using this product

● avoid contamination

● do not reuse. Once opened, discard.

Ask a doctor if you have

● eye pain

● changes in vision

● redness or irritation of the eye after use

● an injury caused by alkali

Keep out of reach of children

- If swallowed, get medical help or contact a Poison Control Center right away.

Directions

- do not dilute solution or reuse bottle
- use only unopened bottle
- to open, twist cap in the direction of the arrow
- avoid contamination of the integrated eyecup
- place integrated eyecup over affected eye(s)
- tilt head backward
- open eyelid(s) wide
- control rate of flow by pressure on bottle
- thoroughly bathe eye(s) with solution
- allow solution to flow away from eye(s)
- rinse until the bottle is empty and continue rinsing with Plum Emergency Eyewash until you reach a doctor
- continue rinsing with water if necessary
- obtain medical treatment.

Other information

- not for use as a contact lens solution
- do not use after bottle expiration
- store at room temperature, 5° to 35° C (41° to 95°F)

Inactive ingredients

Sodium phosphate dibasic, Monopotassium phosphate

Questions or Comments?

Call toll-free number 1-844-405-7233

Distributed by

Innovative Safety Supply USA / 8525 Zionsville Rd. / Indianapolis, IN / 46268 / 18444057233

Principal Display Panel

NDC : 72598-095-20

Plus Rinse

pH Neutral

Emergency Eyewash

Compliance: ANSI/ISEA Z358.1-2009

(As Personal Eyewash Only)

Innovative Safety Supply

Labeler: Innovative Safety Supplu Inc., 368 Edson St. / Saskatoon, SK / S7J0P9 / Canada / 18444057233

Sterile - 200 ml (6.8 fl oz)

Code: 45911

NDC : 72598-095-50

Plus Rinse

pH Neutral

Emergency Eyewash

Compliance: ANSI/ISEA Z358.1-2009

(As Personal Eyewash Only)

Innovative Safety Supply

Labeler: Innovative Safety Supplu Inc., 368 Edson St. / Saskatoon, SK / S7J0P9 / Canada / 18444057233

Sterile - 500 ml (16.9 fl oz)

Code: 45528